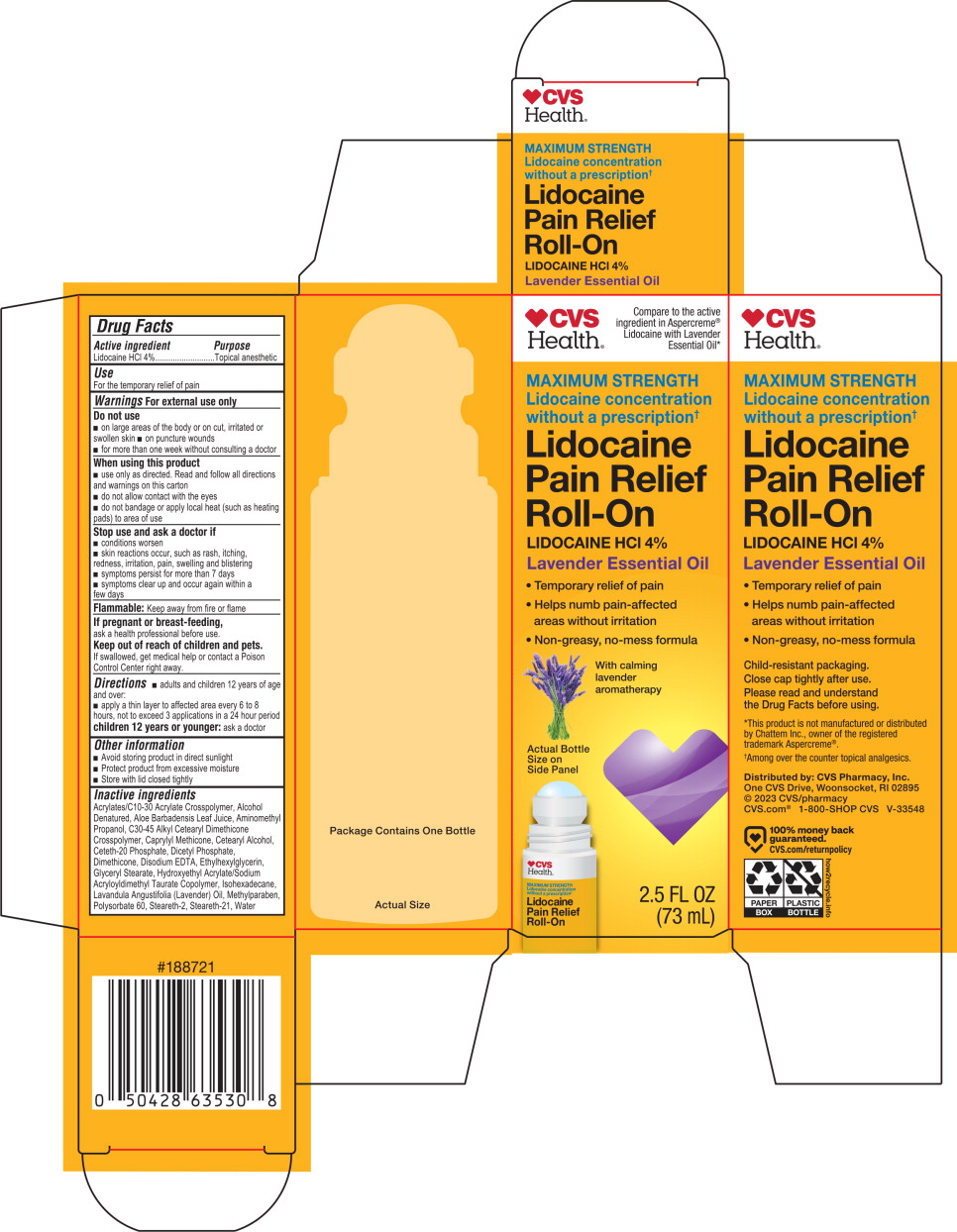 DRUG LABEL: CVS Pain Relief Roll-On Lidocaine with Lavender
NDC: 51316-273 | Form: LOTION
Manufacturer: CVS Pharmacy
Category: otc | Type: HUMAN OTC DRUG LABEL
Date: 20260212

ACTIVE INGREDIENTS: LIDOCAINE HYDROCHLORIDE 40 mg/1 mL
INACTIVE INGREDIENTS: ACRYLATES/C10-30 ALKYL ACRYLATE CROSSPOLYMER (60000 MPA.S AT 0.5%); ALCOHOL; ISOHEXADECANE; WATER; CETETH-20 PHOSPHATE; CAPRYLYL METHICONE; C30-45 ALKYL CETEARYL DIMETHICONE CROSSPOLYMER; LAVENDER OIL; POLYSORBATE 60; DIMETHICONE; ETHYLHEXYLGLYCERIN; ALOE VERA LEAF JUICE; DICETYL PHOSPHATE; GLYCERYL STEARATE; STEARETH-21; EDETATE DISODIUM; METHYLPARABEN; AMINOMETHYL PROPANOL; CETEARYL ALCOHOL; STEARETH-2; HYDROXYETHYL ACRYLATE/SODIUM ACRYLOYLDIMETHYL TAURATE COPOLYMER (100000 MPA.S AT 1.5%)

CVS Lidocaine Lavender Roll On

Active ingredient

Lidocaine HCl 4%

Purpose

Topical anesthetic

Use

For the temporary relief of pain

Warnings

For external use only

Do not use

- on large areas of the body or on cut, irritated, or swollen skin
- on puncture wounds
- for more than one week without consulting a doctor

When using this product

- use only as directed. Read and follow all directions and warnings on this carton
- do not allow contact with the eyes
- do not bandage or apply local heat (such as heating pads) to area of use

Stop use and ask a doctor if

- conditions worsen
- skin reactions occur, such as rash, itching, redness, irritation, pain, swelling and blistering
- symptoms persis for more than 7 days
- symptoms clear up and occur again within a few days

If pregnant or breast-feeding,

ask a health professional before use.

Keep out of reach of children and pets.

If swallowed, get medical help or contact a Poison Control Center right away.

Directions

- adults and children 12 years of age and over:
- apply a thin layer to affected area every 6 to 8 hours, not to exceed 3 applications in a 24 hour period
- children 12 years or younger: ask a doctor

Other information

- Avoid storing the product in direct sunlight
- Protect product from excessive moisture
- Store with lid closed tightly

Inactive ingredients

Acrylates/C10-30 Acrylate Crosspolymer, Alcohol Denatured, Aloe Barbadensis Leaf Juice, Aminomethyl Propanol, C30-45 Alkyl Cetearyl Dimethicone Crosspolymer, Caprylyl Methicone, Cetearyl Alcohol, Ceteth-20 Phosphate, Dicetyl Phosphate, Dimethicone, Disodium EDTA, Ethylhexylglycerin, Glyceryl Stearate, Hydroxyethyl Acrylate/Sodium Acryloyldimethyl Taurate Copolymer, Isohexadecane, Lavandula Angustifolia (Lavender) Oil, Methylparaben, Polysorbate 60, Steareth-2, Steareth-21, Water

Principal Display Panel - 73 mL Carton

CVS Health®

Compare to the active ingredient in Aspercreme® Lidocaine with Lavender Essential Oil*

Maximum Strength

Lidocaine concentration

without a prescription†

Lidocaine Pain Relief Roll-On

Lidocaine HCL 4%

Lavender Essential Oil

- Temporary relief of pain
- Helps numb pain-affected areas without irritation
- Non-greasy, no-mess formula

with claming lavender aromatherapy

Actual Bottle Size on Side Panel

2.5 FL OZ

(73 mL)